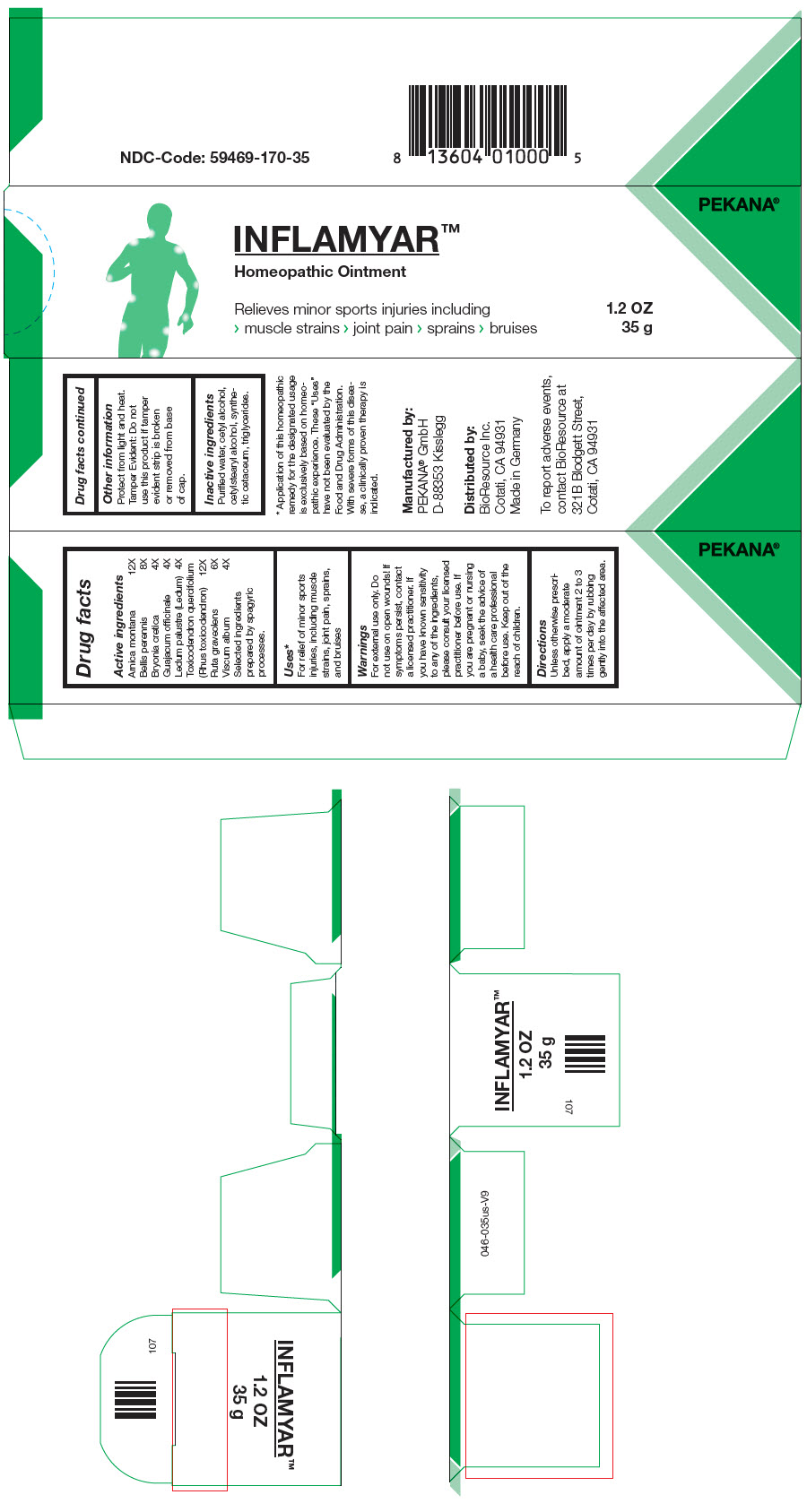 DRUG LABEL: Inflamyar
NDC: 59469-170 | Form: OINTMENT
Manufacturer: Pekana-Naturheilmittel GmbH
Category: homeopathic | Type: HUMAN OTC DRUG LABEL
Date: 20221214

ACTIVE INGREDIENTS: ARNICA MONTANA WHOLE 12 [hp_X]/35 g; BELLIS PERENNIS WHOLE 8 [hp_X]/35 g; bryonia dioica root 4 [hp_X]/35 g; guaiacum officinale resin 4 [hp_X]/35 g; RHODODENDRON TOMENTOSUM LEAFY TWIG 4 [hp_X]/35 g; toxicodendron pubescens leaf 12 [hp_X]/35 g; ruta graveolens flowering top 6 [hp_X]/35 g; viscum album fruit 4 [hp_X]/35 g
INACTIVE INGREDIENTS: water; cetyl alcohol; cetostearyl alcohol; medium-chain triglycerides; cetyl esters wax

INFLAMYAR™
Homeopathic Ointment

Drug facts

ACTIVE INGREDIENT

PURPOSE

Active ingredients
Arnica montana | 12X
Bellis perennis | 8X
Bryonia cretica | 4X
Guajacum officinale | 4X
Ledum palustre (Ledum) | 4X
Toxicodendron quercifolium (Rhus toxicodendron) | 12X
Ruta graveolens | 6X
Viscum album | 4X

Selected ingredients prepared by spagyric processes.

Uses [Application of this homeopathic remedy for the designated usage is exclusively based on homeopathic experience. These "Uses" have not been evaluated by the Food and Drug Administration. With severe forms of this disease, a clinically proven therapy is indicated.]

For relief of minor sports injuries, including muscle strains, joint pain, sprains, and bruises

Warnings

For external use only. Do not use on open wounds! If symptoms persist, contact a licensed practitioner. If you have known sensitivity to any of the ingredients, please consult your licensed practitioner before use. If you are pregnant or nursing a baby, seek the advice of a health care professional before use.

Keep out of the reach of children.

Directions

Unless otherwise prescribed, apply a moderate amount of ointment 2 to 3 times per day by rubbing gently into the affected area.

Other information

Protect from light and heat.

Tamper Evident

Do not use this product if tamper evident strip is broken or removed from base of cap.

Inactive ingredients

Purified water, cetyl alcohol, cetylstearyl alcohol, synthetic cetaceum, triglycerides.

Manufactured by:
PEKANA® GmbH
D-88353 Kisslegg

Distributed by:
BioResource Inc.
Cotati, CA 94931

PRINCIPAL DISPLAY PANEL - 1.2 OZ Tube Carton

PEKANA®

INFLAMYAR™

Homeopathic Ointment

Relieves minor sports injuries including
> muscle strains > joint pain > sprains > bruises

1.2 OZ
35 g